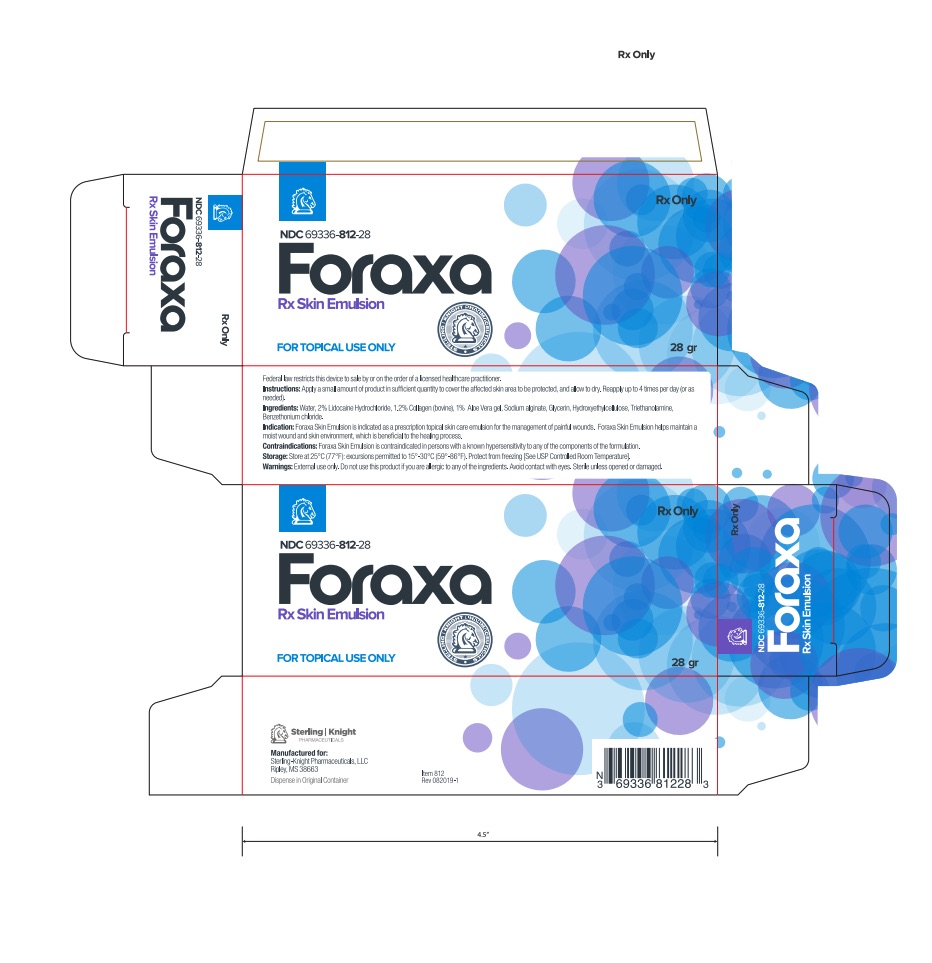 DRUG LABEL: Foraxa Rx Skin Emulsion
NDC: 69336-812
Manufacturer: Sterling-Knight Pharmaceuticals, LLC
Category: other | Type: PRESCRIPTION MEDICAL DEVICE LABEL
Date: 20191108

Foraxa Rx Skin Emulsion

DESCRIPTION

Foraxa Rx Emulsion is a soothing wound gel that promotes a moist wound environment that is ideal for the healing process.

INDICATIONS & USAGE

Foraxa Rx Skin Emulsion is indicated as a prescription topical skin care emulsion for the management of painful wounds. Foraxa Rx Skin Emulsion helps maintain a moist wound and skin environment, which is beneficial to the healing process.

Directions: Apply a small amount of Foraxa Rx Emulsion in sufficient quantity to cover the affected skin area to be protected, and allow to dry. Reapply up to 4 times per day (or as needed).

WARNINGS

External use only. Do not use this product if you are allergic to any of the ingredients. Avoid contact with eyes. Sterile unless opened or damaged.

PRECAUTIONS:

Federal law restricts this device to sale by or on the order of a licensed healthcare practitioner.

CALL YOUR DOCTOR ABOUT SIDE EFFECTS.
Call your doctor about side effects. You may report side effects to Sterling Knight Pharmaceuticals, LLC at 1-888-460-1531 or the FDA at 1-800-FDA-1088.

INSTRUCTIONS FOR USE

Apply a small amount of Foraxa Rx Emulsion in sufficient quantity to cover the affected skin area to be protected, and allow to dry. Reapply up to 4 times per day (or as needed).

INGREDIENTS

Water, Collagen, Aloe Vera gel, Lidocaine Hydrochloride, Sodium alginate, Glycerin, Hydroxyethylcellulose, Triethanolamine, Benzethonium chloride.

HOW SUPPLIED

Foraxa Rx Emulsion is supplied in:
28g tube, NDC 69336-812-28
Distributed By:

Sterling-Knight Pharmaceuticals, LLC
Ripley, MS 38663
Rev 082019-1

STORAGE:

Store at 25°C (77°F): excursions permitted to 15°-30°C (59°-86°F). Protect from freezing [See USP Controlled Room Temperature].